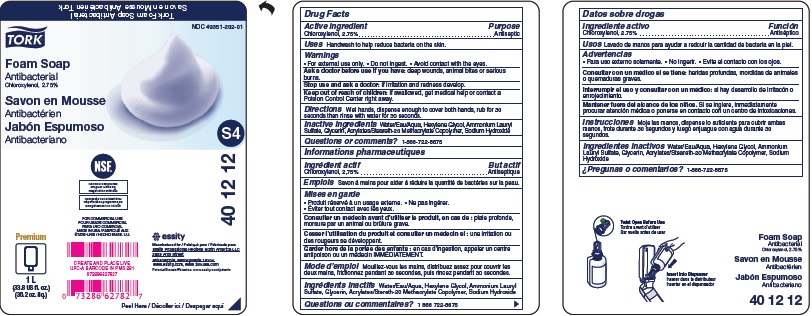 DRUG LABEL: Tork Foam Antibacterial
NDC: 49351-202 | Form: SOAP
Manufacturer: ESSITY NORTH AMERICA INC.
Category: otc | Type: HUMAN OTC DRUG LABEL
Date: 20181214

ACTIVE INGREDIENTS: CHLOROXYLENOL 2.75 g/100 mL
INACTIVE INGREDIENTS: WATER; GLYCERIN; ETHYL ACRYLATE/METHACRYLIC ACID/STEARETH-20 METHACRYLATE COPOLYMER; HEXYLENE GLYCOL; AMMONIUM LAURYL SULFATE; SODIUM HYDROXIDE

Drug Facts

Active ingredient

Chloroxylenol, 2.75%

Purpose

Antiseptic

Uses

Handwash to help reduce bacteria on the skin.

Warnings

For external use only. Do not ingest. Avoid contact with the eyes.

Ask a doctor before use if you have

deep wounds, animal bites or serious burns.

Stop use and ask a doctor

if irritation and redness develop.

Keep out of reach of children

if swallowed, get medical help or contact a Poison Control Center right away.

Directions

Wet hands, dispense enough to cover both hands, rub for 30 seconds then rinse with water for 30 seconds.

Inactive ingredients

Water/Eau/Aqua, Hexylene Glycol, Ammonium Lauryl Sulfate, Glycerin, Acrylates/Steareth-20 Methacrylate Copolymer, Sodium Hydroxide

Questions or Comments?

1-866-722-8675

PACKAGE LABEL

Tork Foam Soap Antibacterial

Savon Mousse Antibacterien Tork

NDC 49351-202-01

TORK

Foam Soap

Antibacterial

Chloroxylenol, 2.75%

Savon en Mousse

Antibacterien

Jabon Espumoso

Antibacteriano

S4

40 12 12

essity

Manufactured for / Fabrique pour / Fabricado para

Essity Professional Hygiene North America LLC

2929 Arch Street

Philadelphia, PA 19104

www.essity.com, www.torkusa.com

Patents/Brevets/Patentes: www.essity.com/patents

Premium

1L

(33.8 US fl. oz.)

(35.2 oz. liq.)

NSF

FOR COMMERCIAL USE

POUR USAGE COMMERCIAL

PARA USO COMMERCIAL

MADE IN USA / FABRIQUE AUX

ETATS-UNIS / HECHO EN EE. UU.

Peel here / Decoller ici / Despegar aqui